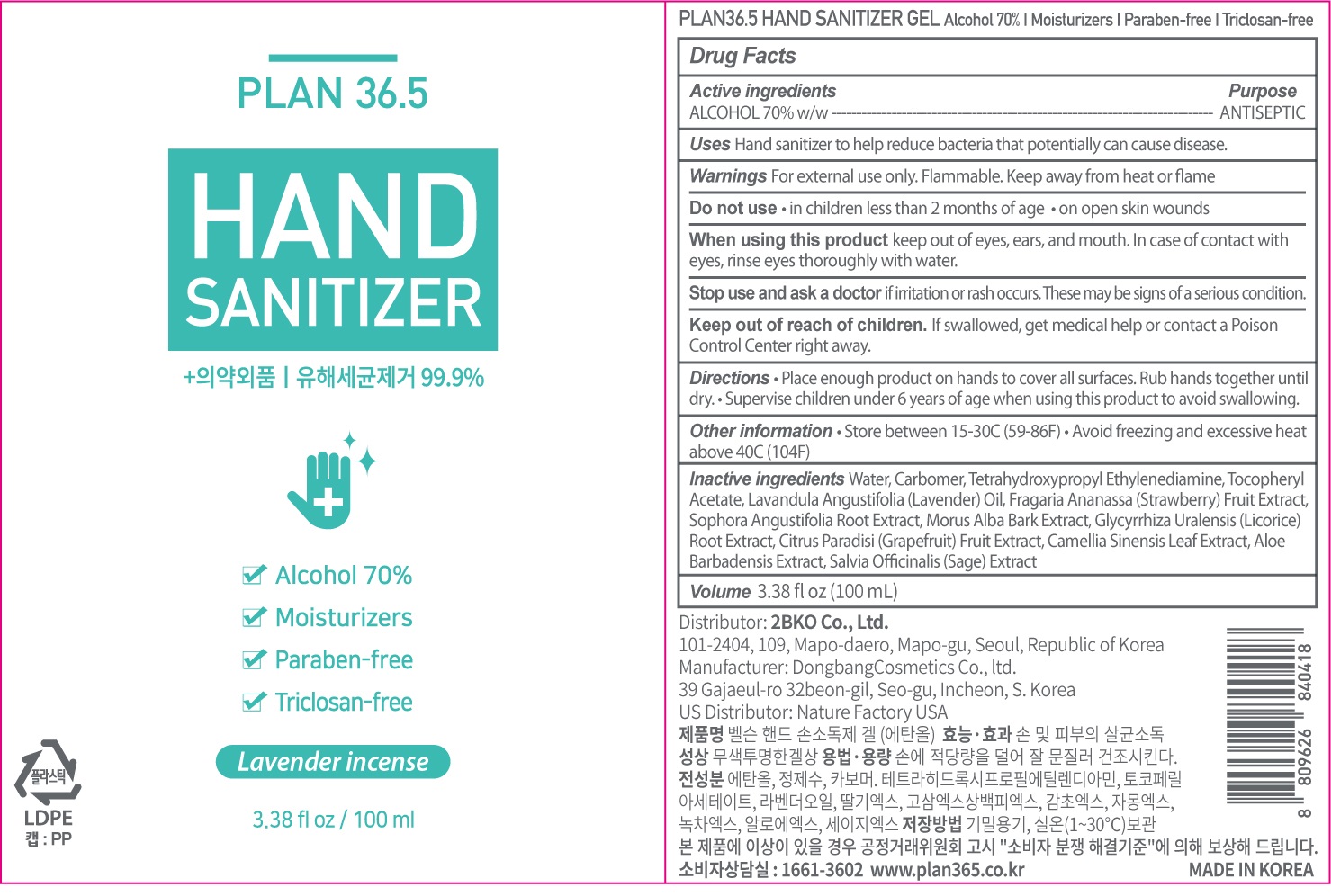 DRUG LABEL: PLAN 36.5 HAND SANITIZER
NDC: 73264-012 | Form: GEL
Manufacturer: 2bko
Category: otc | Type: HUMAN OTC DRUG LABEL
Date: 20200507

ACTIVE INGREDIENTS: ALCOHOL 70 mL/100 mL
INACTIVE INGREDIENTS: Water; CARBOMER HOMOPOLYMER, UNSPECIFIED TYPE; EDETOL; .ALPHA.-TOCOPHEROL ACETATE; LAVENDER OIL; SOPHORA FLAVESCENS ROOT; MORUS ALBA BARK; GLYCYRRHIZA URALENSIS ROOT; GRAPEFRUIT; GREEN TEA LEAF; ALOE VERA LEAF; SALVIA OFFICINALIS ROOT

ACTIVE INGREDIENT

Active ingredient: ALCOHOL 70% w/w

INACTIVE INGREDIENT

Inactive ingredients:

Water, Carbomer, Tetrahydroxypropyl Ethylenediamine, Tocopheryl Acetate, Lavandula Angustifolia (Lavender) Oil, Fragaria Ananassa (Strawberry) Fruit Extract, Sophora Angustifolia Root Extract, Morus Alba Bark Extract, Glycyrrhiza Uralensis (Licorice) Root Extract, Citrus Paradisi (Grapefruit) Fruit Extract, Camellia Sinensis Leaf Extract, Aloe Barbadensis Extract, Salvia Officinalis (Sage) Extract

PURPOSE

Purpose: ANTISEPTIC

WARNINGS

For external use only. Flammable. Keep away from heat or flame
--------------------------------------------------------------------------------------------------------
Do not use
• in children less than 2 months of age
• on open skin wounds
--------------------------------------------------------------------------------------------------------
When using this product keep out of eyes, ears, and mouth. In case of contact with eyes, rinse eyes thoroughly with water.
--------------------------------------------------------------------------------------------------------
Stop use and ask a doctor if irritation or rash occurs. These may be signs of a serious condition.

KEEP OUT OF REACH OF CHILDREN

If swallowed, get medical help or contact a Poison Control Center right away.

Uses

Hand sanitizer to help reduce bacteria that potentially can cause disease.

Directions

• Place enough product on hands to cover all surfaces. Rub hands together until dry.
• Supervise children under 6 years of age when using this product to avoid swallowing.

Other information

• Store between 15-30C (59-86F)
• Avoid freezing and excessive heat above 40C (104F)